DRUG LABEL: Standardized Cat Hair
NDC: 49288-0121 | Form: INJECTION, SOLUTION
Manufacturer: Antigen Laboratories, Inc.
Category: prescription | Type: HUMAN PRESCRIPTION DRUG LABEL
Date: 20090824

ACTIVE INGREDIENTS: FELIS CATUS HAIR 10000 [BAU]/1 mL
INACTIVE INGREDIENTS: Glycerin 0.525 mL/1 mL; Water; Sodium Chloride 0.0095 g/1 mL; Sodium Bicarbonate 0.0024 g/1 mL

Allergenic Extract

WARNINGS
Standardized cat hair and cat pelt extracts labeled in Bioequivalent Allergy Units (BAU/ml) are not interchangeable with each other and are not interchangeable with cat extracts labeled in Allergy Units (AU/ml). Standardized Cat allergenic extract is intended for use by physicians who are experienced in the administration of allergenic extracts for diagnosis, immunotherapy and the emergency care of anaphylaxis, or for use under the guidance of an allergy specialist. This extract is not directly interchangeable with other allergenic extracts. Patients being switched from other types of extract to Antigen Laboratories’ allergenic extracts should be started as though they were coming under treatment for the first time. See “WARNINGS” section. As with all allergenic extracts, severe systemic reactions may occur. In certain individuals, these life-threatening reactions may result in death. Patients should be observed for at least 20 minutes following allergenic extract injections. Treatment and emergency measures, as well as personnel trained in their use, should be immediately available in the event of a life-threatening reaction. Sensitive patients may experience severe anaphylactic reactions resulting in respiratory obstruction, shock, coma and/or death. Patients being switched from one lot of extract to another from the same manufacturer should have the dose reduced by 75%.
This product should not be injected intravenously. Deep subcutaneous routes have proven to be safe, see “WARNINGS”, “PRECAUTIONS”, “ADVERSE REACTIONS” and “OVERDOSAGE” sections.
Patients receiving beta-blockers may not be responsive to epinephrine or inhaled bronchodilators. Respiratory obstruction not responding to parenteral or inhaled bronchodilators may require theophylline, oxygen, intubation and the use of life support systems. Parenteral fluid and/or plasma expanders may be utilized for treatment of shock. Adrenocorticosteroids may be administered parenterally or intravenously. Refer to “ADVERSE REACTIONS” section.

DESCRIPTION
The cat allergen that seems to be most important has been called cat allergen 1 (Fel d I) and is found in saliva and extracts of cat hair, dander, and pelt. Using immunofluorescence, it was shown that this allergen is present in certain sebaceous glands of the skin. It is not found in serum or bladder-puncture urine. There are significant amounts of different non-Fel d I allergens contained in cat pelt extracts that are not present, or present in minimal amounts, in cat hair extracts.
The extract is a sterile solution intended for dilution prior to skin testing and/or immunotherapy. The designation BAU/ml (bioequivalent allergy units per ml) is unitage based upon quantitative skin testing.^23 When the extract contains 10-19.9 Fel d I u/ml, quantitative skin testing indicates it contains 10,000 BAU/ml, 5,000 BAU/ml = 5.00 to 9.99 FDA units of Fel d I.
The source material is cat hair and cat washings. The extracting fluid contains Sodium Chloride 0.95%, Sodium Bicarbonate 0.24%, and Glycerine 50% v/v as a stabilizing agent and preservative. The following is a brief description of the standardized quality procedures applied to these extracts:
1. The source material is carefully selected from healthy, veterinarian inspected cats who react negative to feline leukemia tests.
2. Isoelectric focusing (IEF) comparing Antigen Laboratories’ Standardized Cat Hair 10,000 BAU/ml with the Center for Biologics Evaluation and Research Standardized Cat Hair demonstrates undetectable to minimal cat albumin.
3. Skin testing by ID50EAL method.^23
4. A ninhydrin protein analysis is completed.
5. Each lot is standardized with the Cat (Fel d I) reference standard.
6. The standardized extract is analyzed for glycerine content to insure a minimum 50% v/v glycerine for optimal stability during the entire dating period.

CLINICAL PHARMACOLOGY
As a consequence of the discovery of IgE and the development of methods to identify and quantify anti-allergen IgE levels, interest in recent years has centered around the utilization of in vivo and in vitro diagnostic procedures.^3,5
The most clinically relevant mechanism of mast cell mediator release results from the cross-linking of plasma membrane receptor-bound IgE molecules by specific antigens. In vitro this process is temperature dependent, requires the presence of divalent cations, and also requires activation of a cell membrane-associated serine esterase. Another immunologic mechanism for mast cell degranulation is mediated by complement-derived anaphylatoxins C3a, C4a and C5a. These low molecular weight peptides presumably stimulate degranulation of mast cells by binding to distinct plasma membrane receptor(s) and are active mast cell secretagogues in human skin in vivo. Several naturally occurring and exogenous agents are also capable of degranulating and/or stimulating mast cells by nonimmunologic mechanisms that may differ from those initiated by antigen-IgE binding.
Stimulation of mast cells leads to the release and generation of a variety of pharmacologically active soluble factors that produce immediate hypersensitivity reactions. These factors include both preformed substances as well as unstored mediators that are produced upon stimulation of these cells. Some mediators are rapidly liberated from mast cell granules (e.g., histamine), whereas others remain granule-associated after release from the cell (e.g., heparin). Products of arachidonic acid metabolism are rapidly produced and released from mast cells following stimulation. In addition to immediate reactions mediated by endogenous mast cell-derived pharmacologic agents, selected patients demonstrate later reactions (i.e., late-phase reactions) at sites of mast cell degranulation. These reactions begin 2 to 8 hours after mediator release and are characterized by granulocyte-rich infiltrates that are followed by accumulations of mononuclear cells. Clinically these late-phase reactions present as inflammatory, infiltrated plaques or nodules.^17
Patients who react to a small quantity of antigen by skin testing, or have a high RAST score, can be classified as highly sensitive. Those who react only to large quantities of antigen, or have a low RAST score, can be classified as less sensitive. It would appear that there is at least a 50,000-fold range between the most and least sensitive individuals. On the other hand, certain patients who do not appear to have elevated quantities of specific anti-allergen IgE, RAST negative, do have positive skin tests and have symptoms of allergic rhinitis. These patients are considerably less sensitive than patients with detectable levels of specific IgE antibody.^6
The mode of action of immunotherapy with allergenic extracts is still under investigation. Increasing subcutaneous injection doses of allergenic extract into patients with allergic disease have been shown to result in both humoral and cellular changes including the production of allergen specific IgG antibodies, the suppression of histamine release from target cells, decrease in circulating levels of antigen specific IgE antibody over long periods of time and suppression of peripheral blood T-lymphocyte cell responses to antigen.^(10, 14, 15)
Of ten patients with clinical symptoms from exposure to cats, the ID50EAL skin test results were as follows: Mean sum puncture erythema – 70.4 mm; Range 51-105 mm; Mean sum puncture wheal – 15.6 mm; Range 10-22 mm. Mean intradermal dose in BAU for 50 mm sum of erythema response BAU50 0.14 BAU/ml; Range 0.06-0.19 BAU/ml. Using Histamine Phosphate, 2.75 mg/ml containing 1 mg histamine base: Mean sum puncture erythema – 48.5 mm; Range 29-70 mm.

INDICATIONS AND USAGE
Allergenic extract is indicated for diagnostic testing and for the treatment (immunotherapy) of patients whose histories indicate that upon natural exposure to cat allergen, they experience allergic symptoms. Confirmation is determined by skin testing. An orderly approach to the diagnostic use of allergenic extracts usually begins with direct skin testing.

CONTRAINDICATIONS
Do not administer in the presence of diseases characterized by bleeding diathesis. Individuals with autoimmune disease may be at risk of exacerbating symptoms, of the underlying disease, possibly due to routine immunization. Patients who have experienced a recent myocardial infarction may not be tolerant of immunotherapy. Children with nephrotic syndrome probably should not receive injections due to a variety of seemingly unrelated events, such as immunization causing exacerbation of their nephrotic disease.
This product is not intended for the treatment of patients who do not experience allergic symptoms upon natural exposure to the allergen.
Extreme caution is necessary when using diagnostic skin tests or injection treatment in highly sensitive patients, who have experienced severe symptoms or anaphylaxis by natural exposure or previous skin testing or treatment. IN THESE CASES BOTH THE POTENCY FOR SKIN TESTS AND THE ESCALATION OF THE TREATMENT DOSE MUST BE ADJUSTED TO THE PATIENT’S SENSITIVITY AND TOLERANCE.
This product is not intended for treatment of patients who do not manifest immediate hypersensitivity reactions to the allergenic extract following skin testing.

WARNINGS
Allergenic extracts should be used by physicians with experience in maximal dose immunotherapy and treatment of anaphylaxis. Patients receiving beta-blockers may not be responsive to epinephrine or inhaled bronchodilators.
Epinephrine 1:1000 should be available. When changing from one lot to another of allergenic extract, dose adjustment, if indicated, should be based on such considerations, as the results of skin endpoint titration (see “INDICATIONS AND USAGE” section). Patient re-evaluation may be necessary. Injections should never be given intravenously. A 5/8 inch, 25 gauge needle on a sterile syringe will allow deep subcutaneous injection. Precaution of withdrawing the plunger slightly after inserting the needle is advisable to determine if a blood vessel has been entered. DO NOT INJECT INTRAVENOUSLY. Proper measurement of the dose and caution in making the injection will minimize reactions. Adverse reactions to allergenic extracts are usually apparent within 20-30 minutes following injection. Patients should be detained for 20-30 minutes after injection and advised to notify the office immediately if symptoms or reactions occur.
Patients being switched from one lot of extract to another from the same manufacturer should have the dose reduced by 75%. This extract should be temporarily withheld or dosage reduced in the following conditions: 1) flu or other infection with fever; 2) exposure to excessive amounts of allergen prior to injection; 3) rhinitis and/or asthma exhibiting severe symptoms; 4) adverse reaction to previous injection until cause of reaction has been evaluated by the physician supervising the patient’s immunotherapy program.

PRECAUTIONS
General: Immunotherapy must be given under the supervision of a physician. Sterile solutions of vials, syringes, etc. should be used. Aseptic technique should be observed in making dilutions from bulk extracts, skin testing and extracts for treatment. The usual precautions in administering allergenic extracts are necessary. Disposable, sterile syringe and needle should be used for each individual patient to prevent transmission of serum hepatitis, HIV and other infectious agents from one person to another.
Refer to “OVERDOSAGE” section for a description of the treatment of anaphylactic reactions.
Pregnancy Category C: Animal reproduction studies have not been conducted with allergenic extracts. It is not known whether allergenic extracts cause fetal harm during pregnancy or affect reproductive capacity. A systemic reaction to allergenic extracts could cause uterine contractions leading to spontaneous abortion or premature labor. Allergenic extracts should be used during pregnancy only if potential benefit justifies potential risk to fetus.^11
Nursing Mothers: It is not known whether allergenic extracts are excreted in human milk. Because many drugs are excreted in human milk, caution should be exercised when allergenic extracts are administered to a nursing woman.
Pediatric Use: Allergenic extracts have been used routinely in children and no special problems of safety or specific hazards have been found. Children can receive the same dose as adults. However, to minimize the discomfort associated with dose volume it may be advisable to reduce the volume of the dose in half and administer the injection at two different sites.
Carcinogenicity: Long term studies in animals have not been conducted with cat hair allergenic extracts to evaluate carcinogenicity or mutagenicity.
Drug Interactions: Antihistamines and hydroxyzine can significantly inhibit immediate skin test reactions. This effect has been primarily documented when testing was performed within 1-2 hours after drug ingestion. Although partial inhibition of the skin test reaction has been observed for longer periods, it was minor. Epinephrine injection inhibits the immediate skin test reaction for several hours. Patients on delayed absorption antihistamine tablets should be free of such medication for 48 hours. Maintenance dose potency must be established by the physician’s clinical observation and experience.^(6, 13)
Patients with a history of severe sensitivity and markedly positive skin test to high dilutions of the allergenic extract should be started with low doses of highly diluted extract. Pregnancy or a history of prior reactions to allergen immunotherapy dictates the need to start with small quantities of antigen.

ADVERSE REACTIONS
Adverse reactions include, but are not necessarily limited to urticaria, itching, edema of the extremities, respiratory wheezing or asthma, dyspnea, cyanosis, tachycardia, lacrimation, marked perspiration, flushing of the face, neck or upper chest, mild persistent clearing of the throat, hacking cough, or persistent sneezing.
1) Local Reactions
Small amounts of erythema and swelling at the site of injection are common, the extent varying with the patient. Such reactions should not be considered significant unless they persist for at least 24 hours or exceed 50 mm in diameter.
Larger local reactions are not only uncomfortable, but indicate the possibility of a systemic reaction if dosage is increased. In such cases the dosage should be reduced to the last level not causing the reaction and maintained at this level for two or three treatments before cautiously increasing again.
Large, persistent local reactions or minor exacerbations of the patient’s allergic symptoms may be treated by local cold applications and/or the use of oral antihistamines, but they should be considered a warning of possible severe systemic reactions and the need for temporarily reduced dosages.
A mild burning immediately after the injection is to be expected; this usually leaves in 10-20 seconds. Prolonged pain, or pain radiating up the arm, is usually the result of intramuscular injection, making this injection route undesirable. Subcutaneous injection is the recommended route.
2) Systemic Reactions
Systemic reactions may range from mild exaggeration of the patient’s allergic symptoms to anaphylactic reactions. Very sensitive patients may show a rapid response. In some instances, a severe systemic reaction with blood pressure fall and/or shock may occur. Quantitation of patient’s sensitivity combined with careful early observation is essential for safe skin testing and treatment.
With careful attention to dosage and administration, such reactions occur infrequently, but it must be remembered that allergenic extracts are highly potent to sensitive individuals and OVERDOSE could result in anaphylactic symptoms. Therefore, it is imperative that physicians administering allergenic extracts understand and be prepared for the treatment of severe reactions.
Patients receiving beta-blockers may not be responsive to epinephrine or inhaled bronchodilators. The following are commonly prescribed beta-blockers: Levatol, Lopressor, Propanolol Intersol, Propanolol HCL, Blocadren, Propanolol, Inderal-LA, Visken, Corgard, Ipran, Tenormin, Timoptic. Ophthalmic beta-blockers: Betaxolol, Levobunolol, Timolol, Timoptic. Chemicals that are beta-blockers and may be components of other drugs: Acebutolol, Atenolol, Esmolol, Metoprolol, Nadolol, Penbutolol, Pindolol, Propanolol, Timolol, Labetalol, Carteolol.
It cannot be overemphasized that, under certain unpredictable combinations of circumstances, anaphylactic shock is always a possibility. Other possible systemic reaction symptoms are, in varying degrees of severity, fainting, pallor, bradycardia, hypotension, angioedema, cough, wheezing, conjunctivitis, rhinitis, and urticaria.^(13, 14)

OVERDOSAGE
If a systemic or anaphylactic reaction does occur, oxygen by nasal cannula, mask or ambu bag should be first treatment if patient has respiratory distress or asthma. Apply a tourniquet above the site of injection and inject intramuscularly or subcutaneously 0.3 to 0.5 ml of 1:1000 epinephrine-hydrochloride into opposite arm or gluteal area. The dose may be repeated in 5-10 minutes if necessary. Loosen the tourniquet at least every 10 minutes.
The epinephrine HCL 1:1000 dose for infants to 2 years is 0.05 to 0.1 ml; for children 2 to 6 years it is 0.15 ml; for children 6 to 12 years it is 0.2 ml.
Studies on asthmatic subjects reveal that plasma concentrations of theophylline of 5 to 20 ug/ml are associated with therapeutic effects. Toxicity is particularly apparent at concentrations greater than 20 ug/ml. A loading dose of aminophylline of 5.6 mg/kg intravenously followed by 0.9 mg/kg per hour results in plasma concentrations of approximately 10 ug/ml (Mitenko and Ogilvie 1973b; Nicholson and Chick 1973).^4
Other beta-adrenergic drugs such as isoproterenol, isoetharine, or albuterol may be used by inhalation. The usual dose to relieve broncho-constriction in asthma is 0.5 ml or the 0.5% solution for isoproterenol HCL; albuterol is longer acting than isoproterenol by any route of administration. The albuterol inhaler delivers approximately 90 mcg of albuterol from the mouthpiece. The usual dosage for adults and children would be two inhalations repeated every 4 to 6 hours. Isoetharine supplied in the Bronkometer unit delivers approximately 340 mcg isoetharine. The average adult dose is one to two inhalations.
Patients who have been taking a beta-blocker may be unresponsive to epinephrine. Epinephrine or beta-adrenergic drugs (Alupent) may be ineffective. These drugs should be administered even though a beta-blocker may have been taken. The following treatment will be effective whether or not patient is taking a beta-blocker: Aminophylline IV, slow push or drip, Atrovent (Ipratropium bromide) Inhaler, 3 inhalations repeated, Atropine, 0.4 mg/ml, 0.75 to 1.5 ml IM or IV, Solu-Cortef, 100-200 mg IM or IV, Solu-Medrol, 125 mg IM or IV, Glucagon, 0.5-1 mg IM or IV, Benadryl, 50 mg IM or IV, Cimetidine, 300 mg IM or IV, Oxygen via ambu bag.

DOSAGE AND ADMINISTRATION
The current standard method of immunotherapy dates back to Noon. Therapy is begun with a low dose which has been shown to be tolerated by both experience and skin testing. The initial dilution of allergenic extract, starting dose, and progression of dosage must be carefully determined on the basis of the patient’s history and results of skin tests.
The physician who undertakes immunotherapy should be concerned with the degree of sensitivity of the patient. (See “INDICATIONS AND USAGE”.) Strongly positive skin tests may be risk factors for systemic reactions. Less aggressive immunotherapy schedules may be indicated for such patients.
Serial five-fold or ten-fold dilutions of the extract are used to make more dilute extract concentrations. Other concentrations can be prepared by appropriate dilution. In brief, the allergist can prepare any dilution of extract that is considered appropriate for the patient.
Prick-Puncture Testing: To identify cat sensitive individuals and as a safety precaution, it is recommended that a prick or puncture test using a drop of the 10,000 BAU/ml extract concentrate be performed prior to initiating very dilute intradermal testing. Prick (puncture) testing is performed by placing a drop of extract concentrate on the skin and puncturing the skin through the drop with a small needle such as a bifurcated vaccinating needle. The most satisfactory sites on the back for skin testing are from the posterior axillary fold to 2.5 cm from the spinal column, and from the top of the scapula to the lower rib margins. The best areas on the arms are the volar surfaces from the axilla to 2.5 or 5 cm above the wrist, skipping the anticubital space. Glycerinated extracts are recommended for prick testing using the most concentrated dilution. A positive reaction is approximately 10-15 mm erythema with 2.5 mm wheal.
A positive control using Histamine Phosphate is important to identify those patients whose skin may not be reactive due to medications, metabolic or other reasons. A diluent control, if negative, would exclude false-positive reactions due to ingredients in the diluent or patients who have dermatographism.
Smaller, less conclusive reactions may be considered positive in conjunction with a definitive history of symptoms on exposure to the allergen. The more sensitive the patient the higher the probability that he/she will have symptoms related upon natural exposure to the offending Cat allergen. Hence, the importance of good patient history. Less sensitive individuals can be tested intradermally with an appropriately diluted extract. (See Intradermal Testing.)

SERIAL DILUTIONS
APPROXIMATE BAU/ml RESULTING FROM 1:10 DILUTION
OF ALLERGENIC EXTRACT CONCENTRATE
Allergenic Extract Concentrate

DILUTUION # | DILUTION EXPONENT | 10,000 BAU/ML | 5,000 BAU/ML | 1,000 BAU/ML
1 | 10^-1 | 1,000 | 500 | 100
2 | 10^-2 | 100 | 50 | 10
3 | 10^-3 | 10 | 5.0 | 1.0
4 | 10^-4 | 1 | 0.5 | 0.1
5 | 10^-5 | 0.1 | 0.05 | 0.01
6 | 10^-6 | 0.01 | 0.005 | 0.001
7 | 10^-7 | 0.001 | 0.0005 | 0.0001
8 | 10^-8 | 0.0001 | 0.00005 | 0.00001
9 | 10^-9 | 0.00001 | 0.000005 | 0.000001
10 | 10^-10 | 0.000001 | 0.0000005 | 0.0000001

SERIAL DILUTIONS
APPROXIMATE BAU/ml RESULTING FROM 1:5 DILUTION
OF ALLERGENIC EXTRACT CONCENTRATE
Allergenic Extract Concentrate

DILUTION # | DILUTION EXPONENT | 10,000 BAU/ML | 5,000 BAU/ML | 1,000 BAU/ML
1 | 5^-1 | 2,000 | 1,000 | 200
2 | 5^-2 | 400 | 200 | 40
3 | 5^-3 | 80 | 40 | 8.0
4 | 5^-4 | 16 | 8.0 | 1.6
5 | 5^-5 | 3.2 | 1.6 | 0.32
6 | 5^-6 | 0.64 | 0.32 | 0.064
7 | 5^-7 | 0.128 | 0.064 | 0.0128
8 | 5^-8 | 0.0256 | 0.0128 | 0.00256
9 | 5^-9 | 0.00512 | 0.00256 | 0.000512
10 | 5^-10 | 0.001024 | 0.000512 | 0.0001024

Intradermal testing: The surface of the upper and lower arm is the usual location for skin testing. It is important that a new sterile, disposable syringe and needle be used for each extract tested. Intracutaneous test dilutions should be made with aqueous diluent. Three-fold, five-fold or ten-fold dilutions may be prepared from stock concentrate extract. (1) Start testing with the most dilute allergenic extract concentration. (2) A volume of 0.01-0.02 ml should be injected slowly into the superficial skin layers making a small bleb (superficial wheal). (3) For patients with a suspected cat sensitivity an allergenic extract dilution of 5^-10 (0.005 BAU/ml) or 10^-7 (0.001 BAU/ml) dilution should be used for initial skin testing. Sensitivity of the patient can be expressed only if the minimum concentration required for a 1+ or 2+ reaction (see chart below) is determined by performing a skin test titration. The reaction should be read after fifteen minutes.
EVALUATION OF SKIN REACTIONS

GRADE | mm ERYTHEMA | mm WHEAL
0 | less than 5 | less than 5
+/- | 5-10 | 5-10
1+ | 11-20 | 5-10
2+ | 21-30 | 5-10
3+ | 31-40 | 10-15 or with pseudopods
4+ | greater than 40 | greater than 15 or with many pseudopods

If after 20 minutes no skin reaction is obtained, continue the testing using increments in the concentration until a reaction of 5-10 mm wheal and 10-30 mm erythema is obtained, or until the concentration of 5^-2 or 10^-1 has been tested. As a negative control the diluent, a concentration of less than 0.5% glycerine (5^-3 or 10^-3), does not produce positive skin wheal and erythema. The diluent should be tested and included in the interpretation of the skin reactions.^17
INTRADERMAL TESTING--SKIN ENDPOINT TITRATION
The allergenic extract to which the patient is sensitive, the patient’s degree of sensitivity and the initial dose of allergen to be used in immunotherapy can be quantitated using five-fold dilutions of allergenic extract for intracutaneous testing. The critical variable is the size of the wheal and erythema produced by the intracutaneous injection of 0.01-0.02 ml of the test allergen producing a 4 mm diameter superficial wheal. For initial screening 5^-10 (0.005 BAU/ml) is a safe dilution. When a sequence of five-fold or ten-fold dilutions of an allergen are injected, the endpoint is detected by noting the dilution that first produces a wheal and erythema (15 minutes after injection) that is 2 mm larger than wheals with erythema produced by weaker, non-reacting dilutions (5 mm negative wheal). The endpoint dilution is used as a starting dose concentration for immunotherapy.
Normally, immunotherapy with allergenic extracts can be started with 0.15 ml of the endpoint of reaction. In any allergic patient, a safe starting dose can be determined by finding the first dose by intradermal skin testing producing a 1+ reaction or the dilution producing the skin endpoint.
If the first injection of the initial dilution of extract is tolerated without significant local reaction, increasing doses by 5-20% increments of that dilution may be administered. The rate of increase in dosage in the early stages of treatment with highly diluted extracts is usually more rapid than the rate of increase possible with more concentrated extracts. This schedule is intended only as a guide and must be modified according to the reactivity of the individual patient. Needless to say, the physician must proceed cautiously in the treatment of the highly sensitive patient who develops large local or systemic reactions.
Some patients may tolerate larger doses of the allergenic extract depending on patient response.^7 Because dilute extracts tend to lose activity on storage, the first dose from a more concentrated vial should be the same or less than the previous dose.^(8, 12)
Dosages progressively increase thereafter according to the tolerance of the patient at intervals of one to seven days until, (1) the patient achieves relief of symptoms, (2) induration at the site of injection is no larger than 50 mm in 36 to 48 hours, (3) a maintenance dose, the largest dose tolerated by the patient short of aggravating existing symptoms, systemic symptoms, or anaphylaxis, or patient demonstrates untoward reactions that indicate the dose to be excessive. This maintenance dose may be continued at regular intervals perennially. It may be necessary to adjust the progression of dosage downward to avoid local and constitutional reactions.

HOW SUPPLIED
Standardized Cat allergenic extract is expressed in BAU/ml. It is supplied in 10,000 BAU/ml, 5,000 BAU/ml and 1,000 BAU/ml in 5, 10, 30 and 50 ml containers. Extracts in 5 ml dropper bottles are available for prick-puncture testing. To insure maximum potency for the entire dating period, all stock concentrates contain 50% v/v glycerine.

STORAGE
Store all stock concentrates and dilutions at 2-8 degrees C. Keep at this temperature during office use. The expiration date of allergenic extract is listed on the container label. Dilutions of the allergenic extract concentration containing less than 50% v/v glycerine are less stable and, if loss of potency is suspected, it can be checked by skin testing with equal concentrations of a freshly prepared dilution of allergenic extract on known sensitive individuals.

REFERENCES

1. Evans, R., Pence, H., Kaplan, H., Rocklin, R.: The Effect of Immunotherapy on Humoral and Cellular Response in Ragweed Hay Fever. J. Clin. Inv. 57: 1378-1385, 1976.
2. Gleich, G.J., Yunginger, J.W.: The Radio Allergo Sorbent Test: A Method to Measure IgE Antibodies, IgG Blocking Antibodies, and the Potency of Allergy Extracts. Bull., NY Acad, Sci. 57 (7): 559-567, 1981.
3. Allergenic Products: Antigen E. Potency Test: Additional Standards for Miscellaneous Products, 21 CFR Part 680, Federal Register, Vol. 46, No. 147, Friday, July 31, 1981, Rules and Regulations, pp. 39128-39136.
4. Goodman, L.S., Gillman, A.: Editors, The Pharmacological Basis of Therapeutics, MacMillan Publishing Co., Inc., Chapter 19, p. 375.
5. Kniker, W.T.: "Clinical Science and Common Sense in the Diagnosis and Immunotherapy of Respiratory Allergy," Continuing Education for the Family Physician, Vol. 10, No. 5, May 1979, pp. 16-33.
6. Matthews, K., et al: Rhinitis, Asthma and Other Allergic Diseases. NIAID Task Force Report, U.S. Dept. HEW, NIH Publication No. 79-387, Chapter 4, pp. 213-217, May 1979.
7. Ishizaka, K.: Control of IgE Synthesis, Third Edition, Allergy Principles and Practices, Vol. I, Chap. 4, p. 52, Edited by Middleton et al.
8. Nelson, H.S.: "The Effect of Preservatives and Dilution on the Deterioration of Russian Thistle (Salsola pestifer), a pollen extract." The Journal of Allergy and Clinical Immunology, Vol. 63, No. 6, pp. 417-425, June 1979.
9. Norman, P.S., Lichtenstein, L.M., Ishizaka, K.: "Diagnostic Tools in Ragweed Hay Fever: A Comparison of Direct Skin Tests IgE Antibody Measurments and Basophil Histamine Release." The Journal of Allergy and Clinical Immunology, Vol. 52, 1973, pg. 210.
10. Rocklin, R.E. Sheffer, A.L., Grainader, D.K. and Melmon, K.: "Generation of antigen-specific suppressor cells during allergy desensitization", New England Journal of Medicine, Vol. 302, pp. 1213-1219, May 29, 1980.
11. Seebohm, P.M., et al: Panel on Review of Allergenic Extracts, Final Report, Food and Drug Administration, pp. 9-48, March 13, 1981.
12. Stevens, E.: Cutaneous Tests Regulatory Control and Standardization of Allergenic Extracts, First International Paul-Ehrlich Seminar, May 20-22. 1979, Frankfurt, Germany, pp. 133-138.
13. Van Metre, T., Adkinson, N., Amodio, F., Lichtenstein, L., Mardinay, M., Norman, P., Rosenberg, G., Sobotka, A., Valentine, M.: "A Comparative Study of the Effectiveness of the Rinkel Method and the Current Standard Method of Immunology for Ragweed Pollen Hay Fever," The Journal of Clinical Allergy and Immunology, Vol. 66, No. 6, p. 511, December 1980.
14. Wasserman, S.: The Mast Cell and the Inflammatory Response. The Mast Cell - its role in health and disease. Edited by J. Pepys and A.M. Edwards, Proceedings of an International Symposium, Davos, Switzerland, Pitman Medical Publishing Co., pp. 9-20, 1979.
15. Perelmutter, L.: IgE Regulation During Immunotherapy of Allergic Diseases. Annals of Allergy, Vol. 57, August 1986.
16. Baer, H., Anderson, M.C., Turkeltaub, P.C.: Allergenic Extracts, Third Edition, Allergy Principles and Practice, Vol. 1, Chap. 17, pp. 373, 1988.
17. Wasserman, S., Marquart, D.: Anaphylaxis, Third Edition, Allergy Principles and Practice, Vol. 1, Chap. 58, pg. 1365, edited by Middleton et al.
18. Solomon, W., Matthews, K.: Aerobiology and inhalant allergens, Third Edition, Allergy Principles and Practice, Vol. I, Chapt. 16, pg. 312, edited by Middleton et al.
19. Bullock, J., Frick, O.: Mite Sensitivity in House Dust Allergic Children, Am. J. Dis. Child., pp. 123-222, 1972.
20. Kawai, T., Marsh, D., Lichtenstein, L., Norman, P.: The Allergens Responsible for House Dust Allergy. I. Comparison of Dermatophagoides pteronyssinus and House Dust Extracts by Assay of Histamine Release from Allergic Human Leukocytes. J. Allergy Clin. Immunol. 50: 117, 1972.
21. Willoughby, J.W.: Inhalant Allergy Immunotherapy with Standardized and Nonstandardized Allergenic Extracts, American Academy of Otolaryngology-Head and Neck Surgery: Instructional Courses, C.V. Mosby Co., Vol. 1, Chapter 15, September 1988.
22. Allergy Principles and Practice, Third Edition, Vol. I and II, Edited by Middleton, Reed, Ellis, Adkinson, Yunginger, C.V. Mosby Co., 1988.
23. Turkeltaub, P., Rastogi, S., Baer, H.: Office of Biologics Research and Review Skin Test Method for Evaluation of Subject Sensitivity to Standardized Allergenic Extracts and for Assignment of Allergy Units to Reference Preparations Using the ID50EAL Method, 1986.